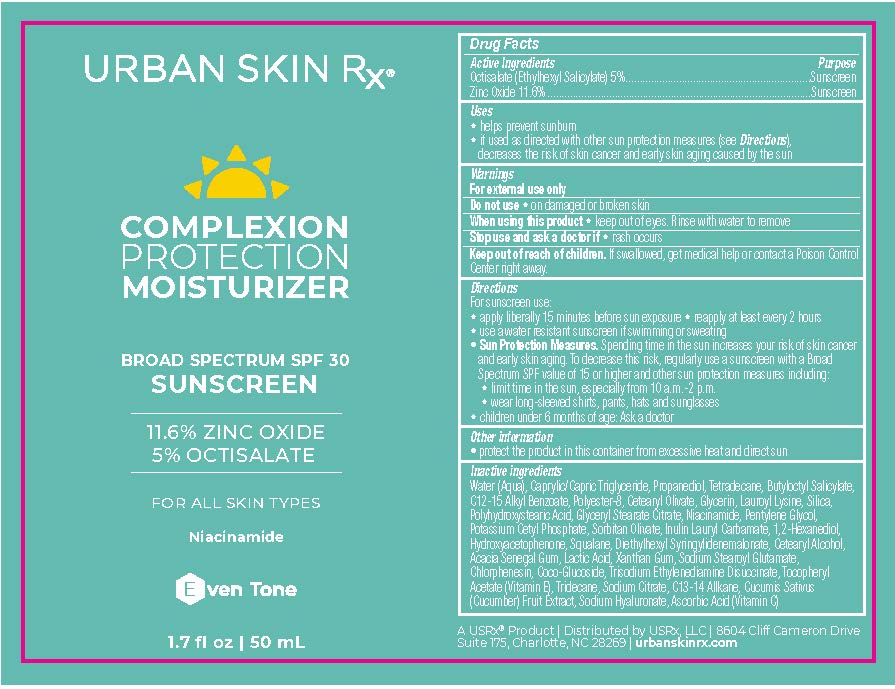 DRUG LABEL: Complexion Protection Moisturizer SPF
NDC: 70809-1912 | Form: CREAM
Manufacturer: USRX LLC
Category: otc | Type: HUMAN OTC DRUG LABEL
Date: 20241001

ACTIVE INGREDIENTS: ZINC OXIDE 11.6 mg/100 mL; OCTISALATE 5 mg/100 mL
INACTIVE INGREDIENTS: INULIN LAURYL CARBAMATE; PROPANEDIOL; BUTYLOCTYL SALICYLATE; LAUROYL LYSINE; NIACINAMIDE; 1,2-HEXANEDIOL; CETOSTEARYL ALCOHOL; LACTIC ACID, L-; CUCUMBER; DIETHYLHEXYL SYRINGYLIDENEMALONATE; CHLORPHENESIN; .ALPHA.-TOCOPHEROL ACETATE; ACACIA; SODIUM STEAROYL GLUTAMATE; TRIDECANE; TRISODIUM CITRATE DIHYDRATE; POLYESTER-8 (1400 MW, CYANODIPHENYLPROPENOYL CAPPED); SILICON DIOXIDE; PENTYLENE GLYCOL; POTASSIUM CETYL PHOSPHATE; POLYHYDROXYSTEARIC ACID (2300 MW); GLYCERYL STEARATE CITRATE; HYDROXYACETOPHENONE; POLY(LAURYLGLUCOSIDE)-7; ASCORBIC ACID; XANTHAN GUM; TETRADECANE; TRISODIUM ETHYLENEDIAMINE DISUCCINATE; WATER; CETEARYL OLIVATE; HYALURONATE SODIUM; GLYCERIN; SQUALANE; SORBITAN OLIVATE; ALKYL (C12-15) BENZOATE; MEDIUM-CHAIN TRIGLYCERIDES

Complexion Protection Moisturizer

PACKAGE LABEL

Active ingredients

Octisalate (Ethylhexyl Salicylate) 5%

Zinc Oxide 11.6%

Purpose

Sunscreen

Uses

- helps prevent sunburn
- if used as directed with ohter sun protection measures (see Directions), decreases the risk of skin cancer and early skin aging caused by the sun

Do not use on damaged or broken skin

When using this product keep out of eyes. Rinse with water to remove

Stop use and ask a doctor if rash occurs

Keep out of reach of children. If swallowed, get medical help or contact a Poison Control Center right away.

Warnings

For external use only

Directions

For sunscreen use:

- apply liberally 15 minutes before sun exposure
- reapply at least every 2 hours
- use a water resistant sunscreen if swimming or sweating
- Sun Protection Measures. Spending time in the sun increases your risk of skin cancer and early skin aging. To decrease this risk, regularly use a sunscreen with a Broad Spectrum SPF value of 15 or higher and other sun protection measures including:
  - limit time in the sun, especially from 10 a.m.-2 p.m.
  - wear lon-sleeved shirts, pants, hats and sunglasses
  - Children under 6 months of age:Ask a doctor

Other information

- protect the product in this container from excessive heat and direct sun

Inactive ingredients

Water (Aqua), Caprylic/Capric Triglyceride, Propanediol, Tetradecane, Butyloctyl Salicylate,
C12-15 Alkyl Benzoate, Polyester-8, Cetearyl Olivate, Glycerin, Lauroyl Lysine, Silica,
Polyhydroxystearic Acid, Glyceryl Stearate Citrate, Niacinamide, Pentylene Glycol,
Potassium Cetyl Phosphate, Sorbitan Olivate, Inulin Lauryl Carbamate, 1,2-Hexanediol,
Hydroxyacetophenone, Squalane, Diethylhexyl Syringylidenemalonate, Cetearyl Alcohol,
Acacia Senegal Gum, Lactic Acid, Xanthan Gum, Sodium Stearoyl Glutamate,
Chlorphenesin, Coco-Glucoside, Trisodium Ethylenediamine Disuccinate, Tocopheryl
Acetate (Vitamin E), Tridecane, Sodium Citrate, C13-14 Allkane, Cucumis Sativus
(Cucumber) Fruit Extract, Sodium Hyaluronate, Ascorbic Acid (Vitamin C)